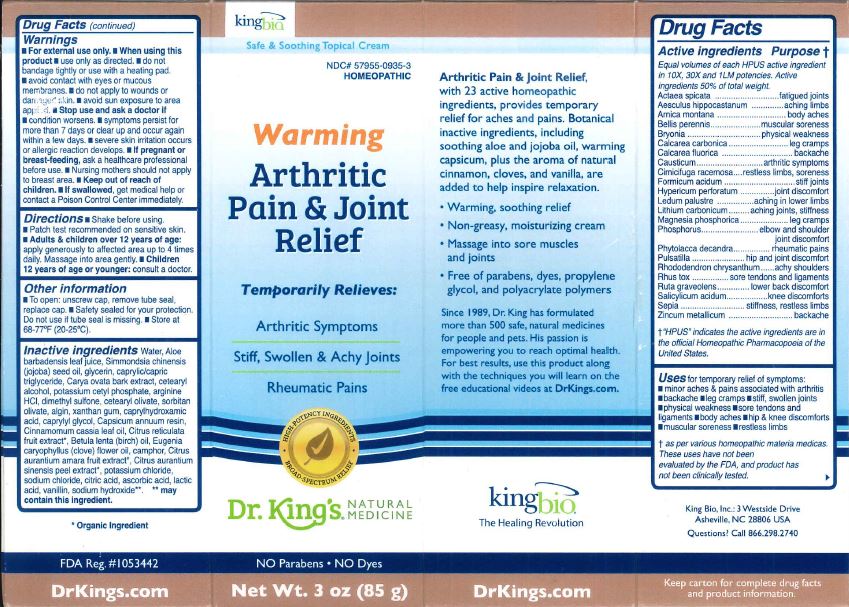 DRUG LABEL: Warming Arthritic Pain and Joint Relief
NDC: 57955-0935 | Form: CREAM
Manufacturer: King Bio Inc.
Category: homeopathic | Type: HUMAN PRESCRIPTION DRUG LABEL
Date: 20181217

ACTIVE INGREDIENTS: ACTAEA SPICATA ROOT 10 [hp_X]/85 g; HORSE CHESTNUT 10 [hp_X]/85 g; ARNICA MONTANA 10 [hp_X]/85 g; BELLIS PERENNIS 10 [hp_X]/85 g; BRYONIA ALBA ROOT 10 [hp_X]/85 g; OYSTER SHELL CALCIUM CARBONATE, CRUDE 10 [hp_X]/85 g; CALCIUM FLUORIDE 10 [hp_X]/85 g; CAUSTICUM 10 [hp_X]/85 g; BLACK COHOSH 10 [hp_X]/85 g; FORMIC ACID 10 [hp_X]/85 g; HYPERICUM PERFORATUM 10 [hp_X]/85 g; RHODODENDRON TOMENTOSUM LEAFY TWIG 10 [hp_X]/85 g; LITHIUM CARBONATE 10 [hp_X]/85 g; MAGNESIUM PHOSPHATE, DIBASIC TRIHYDRATE 10 [hp_X]/85 g; PHOSPHORUS 10 [hp_X]/85 g; PHYTOLACCA AMERICANA ROOT 10 [hp_X]/85 g; ANEMONE PULSATILLA 10 [hp_X]/85 g; RHODODENDRON AUREUM LEAF 10 [hp_X]/85 g; TOXICODENDRON PUBESCENS LEAF 10 [hp_X]/85 g; RUTA GRAVEOLENS FLOWERING TOP 10 [hp_X]/85 g; SALICYLIC ACID 10 [hp_X]/85 g; SEPIA OFFICINALIS JUICE 10 [hp_X]/85 g; ZINC 10 [hp_X]/85 g
INACTIVE INGREDIENTS: WATER; ALOE VERA LEAF; JOJOBA OIL; GLYCERIN; GLYCERYL TRICAPRYLATE; CARYA OVATA BARK; CETOSTEARYL ALCOHOL; POTASSIUM CETYL PHOSPHATE; ARGININE HYDROCHLORIDE; DIMETHYL SULFONE; CETEARYL OLIVATE; SORBITAN OLIVATE; SODIUM ALGINATE; XANTHAN GUM; CAPRYLHYDROXAMIC ACID; CAPRYLYL GLYCOL; CAPSICUM; CHINESE CINNAMON LEAF OIL; TANGERINE JUICE; METHYL SALICYLATE; CLOVE OIL; CAMPHOR LEAF OIL; CITRUS AURANTIUM FRUIT RIND; BITTER ORANGE OIL; POTASSIUM CHLORIDE; SODIUM CHLORIDE; CITRIC ACID MONOHYDRATE; ASCORBIC ACID; LACTIC ACID; VANILLIN; SODIUM HYDROXIDE

Warming Arthritic Pain and Joint Relief

Active Ingredients

Actaea spicata, Aescuculus hippocastanum, Arnica montana, Bellis perennis, Bryonia, Calcarea carbonica, Calcarea fluorica, Causticum, Cimicifuga racemosa, Formicum acidum, Hypericum perforatum, Lithium carbonicum, Magnesia phosphorica, Phosphorus, Phytolacca decandra, Pulsatilla, Rhododendron chrysanthum, Rhus tox, Ruta graveolens, Salicylicum acidum, Sepia, Zincum metallicum

Purpose

Actaea spicata...............................fatigued joints

Aescuculus hippocastanum..............aching limbs

Arnica montana..............................body aches

Bellis perennis................................muscular soreness

Bryonia.........................................physical weakness

Calcarea carbonica.........................leg cramps

Calcarea fluorica............................backache

Causticum....................................arthritic symptoms

Cimicifuga racemosa......................restless limbs, soreness

Formicum acidum..........................stiff joints

Hypericum perfoatum.....................joint discomfort

Lithium carbonicum.......................aching joints, stiffness

Magnesia phosphorica...................leg cramps

Phosphorus..................................elbow and shoulder joint discomfort

Phytolacca decandra......................rheumatic pains

Pulsatilla......................................hip and joint discomfort

Rhododendron chrysanthum...........achy shoulders

Rhus tox......................................sore tendons and ligaments

Ruta graveolens...........................lower back discomfort

Salicylicum acidum.......................knee discomforts

Sepia..........................................stiffness, restless limbs

Zincum metallicum.......................backache

Uses

for temporary relief of symptoms: minor aches & pains associated with arthitis, backache, leg cramps, stiff, swollen joints, physical weakness, sore tendons and ligaments, body aches, hip & knee discomforts, muscular soreness, restless limbs

Warnings

For external use only. When using this product- use ony as directed. do not bandage tightly or use witha heating pad. avoid contact with eyes or mucous membranes. do not apply to wounds or damages skin. avoid sun exposure to area applied. Stop use and ask a doctor if- condition worsens. smptoms persist for more than 7 dayd or clear up and occur again within a few days. severe skin irritation occurs or allergic reaction develops. If pregnant or breast-feeding, ask a healthcare professional before use. Nursing mothers should not apply to breast area. Keep out of reac of children. If swallowed, b get medical help or contact a Poison Control Center immediately.

Keep out of reach of children.

Directions

Shake before using. Patch test recommended on sensitive skin. Adults & Children over 12 years of age: apply generously to affected area up to 4 times daily. Massage into area gently. Children 12 years f age or younger: consult a doctor.

Other Information

To open: unscrew cap, remove tube seal, replace cap. Safety sealed for your protection. Do not use if tube seal is missing. Store at 68-77 degrees Fahrenheit (20-25 degrees Celsius)

Inactive Ingredients

Water, Aloe barbadensis leaf juice, Simmondsia chinensis (jojoba) seed oil, glycerin, caprylic/capric triglyceride, Carya ovata bark extract, cetearyl alcohol, potassium cetyl phosphate, arginine HCL, dimethyl sulfone, ceteayl olivate, sorbitan olivate algin, xanthan gum, caprylhydroxamic acid, caprylyl glycol, Capsicum annuum resin, Cinnamomum cassia leaf oil, Citrus reticulata fruit extract, Betula lenta (birch) oil, Eugenia cayopyllus (clove) flower oil, camphor, Citrus aurantium amara fruit extract, Citrus aurantium sinensis peel extract, potassium chloride, sodium chloride, citric acid, ascorbic acid, lactic acid, vanillin, sodium hydroxide.